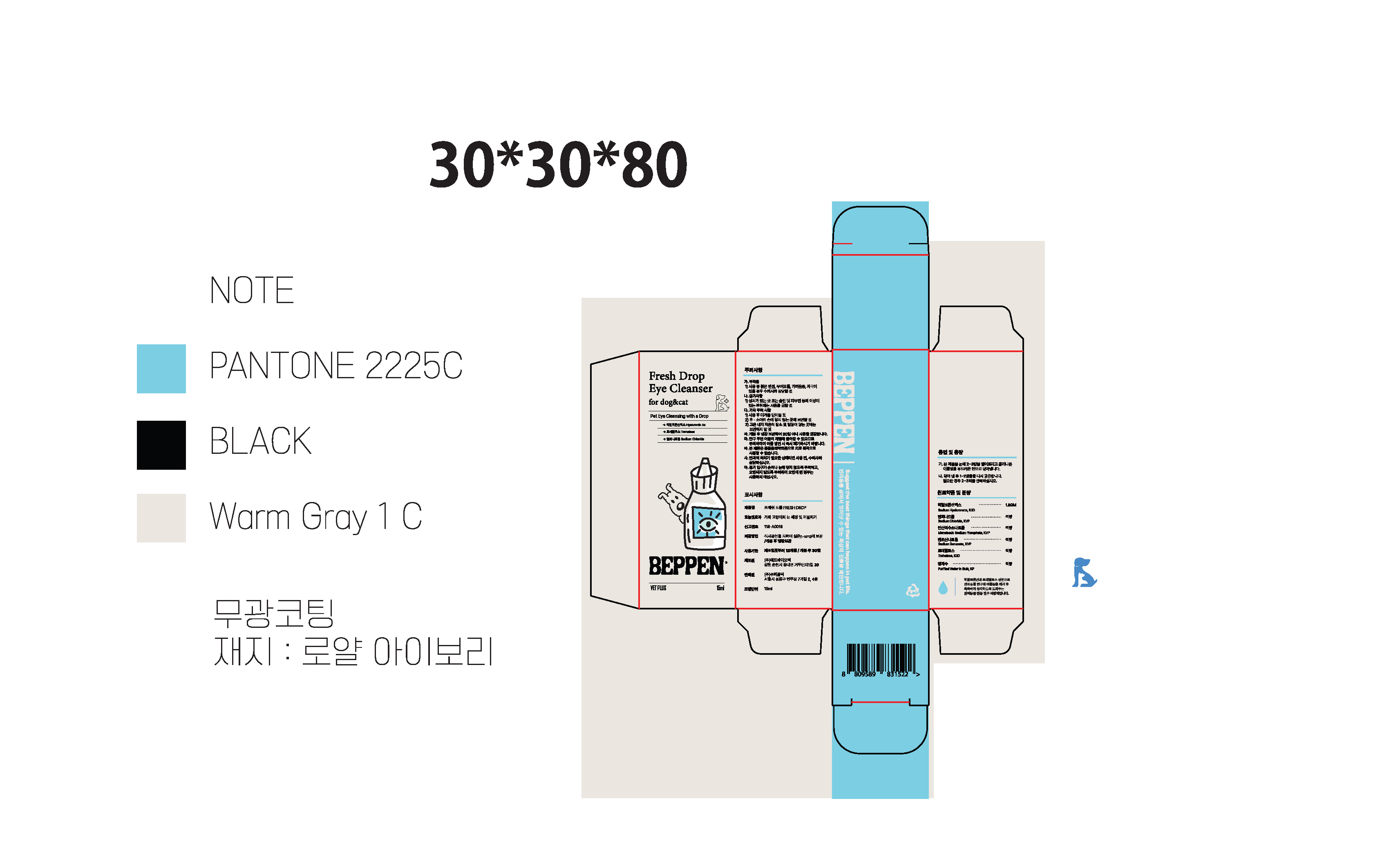 DRUG LABEL: BEPPEN FRESH DROP
NDC: 86243-0003 | Form: LIQUID
Manufacturer: SUPERBLIC Inc.
Category: animal | Type: OTC ANIMAL DRUG LABEL
Date: 20250902

ACTIVE INGREDIENTS: SODIUM HYALURONATE 0.18 g/1 mL
INACTIVE INGREDIENTS: WATER; TREHALOSE

ACTIVE INGREDIENT

SODIUM HYALURONATE

INACTIVE INGREDIENT

SODIUM CHLORIDE

DIBASIC POTASSIUM PHOSPATE

SODIUM BENZOATE

WATER

PURPOSE

Pet eye care: cleaning and removal of irritants for dogs and cats

Keep out of reach of children

INDICATIONS AND USAGE

Apply 2-3 drops of this product to your eye and wipe away any foreign matter with a soft cloth.

After wiping, reapply 1-2 drops.

Repeat 2-3 times if necessary.

WARNINGS

Precautions
A. Side Effects
1) If red spots, swelling, itchiness, or irritation occur during use, consult a veterinarian.

B. Contraindications
1) Do not use on wounds, eczema, or other skin abnormalities.

C. Other Precautions
1) Close the cap after use.
2) Keep out of reach of infants and children.
3) Do not store in extremely hot or cold places or in direct sunlight.

D. If foreign substances appear, do not use and discard immediately.

E. Store in a cool place out of direct sunlight or in the refrigerator.
F. This product is a veterinary drug and cannot be used for therapeutic purposes.
G. If ophthalmic treatment is required, consult a veterinarian before use.
H. Be careful not to let the container's opening touch your hands or eyes. Do not contaminate it. Do not use if contaminated.
I. When opening, be careful not to let the tip of the container come into direct contact with your eyes, as the cut edge may be sharp.
J. After opening, it is recommended to discard the first 1-2 drops before use.

DOSAGE AND ADMINISTRATION

For external use only